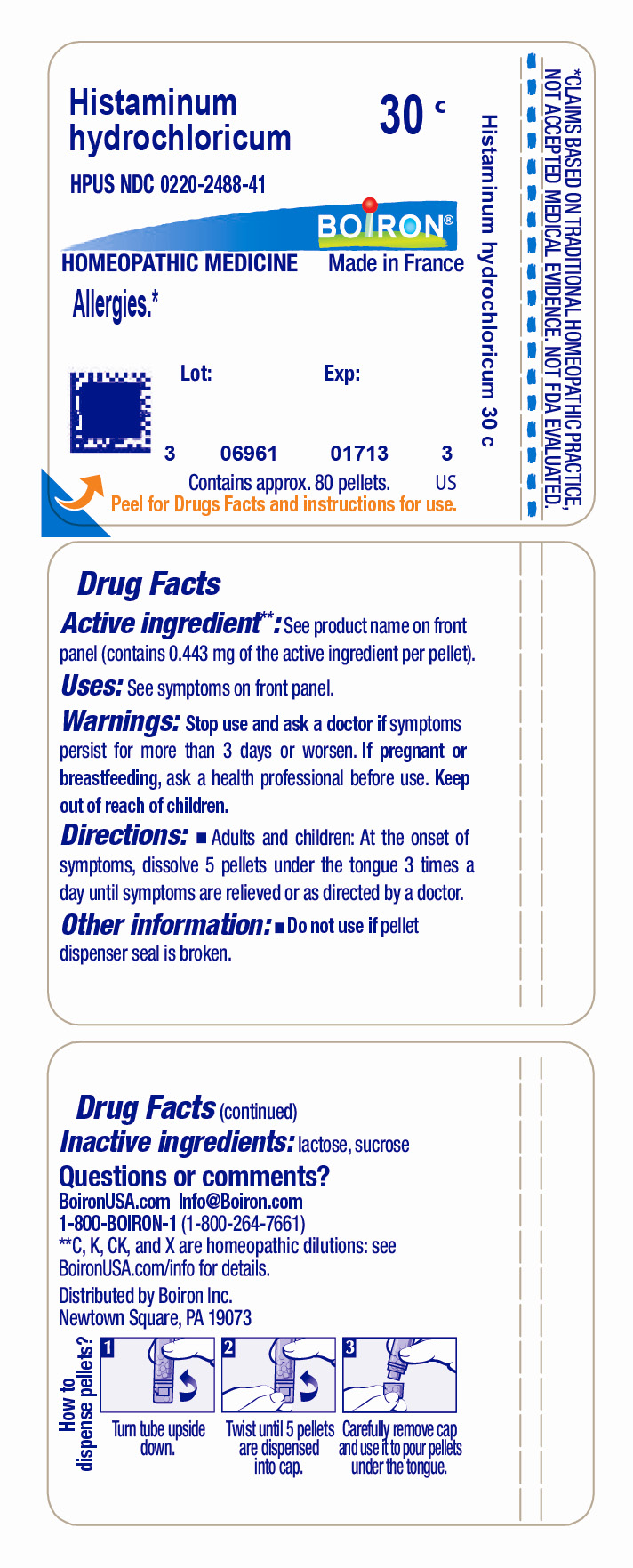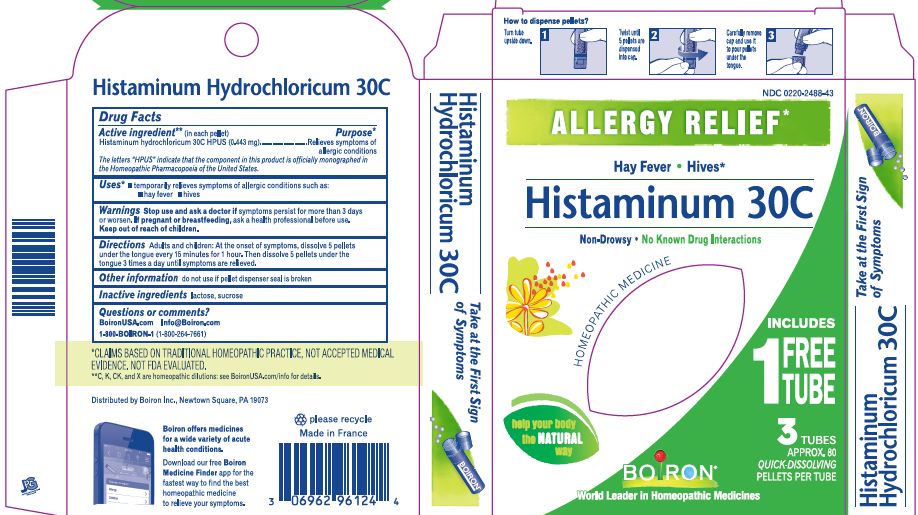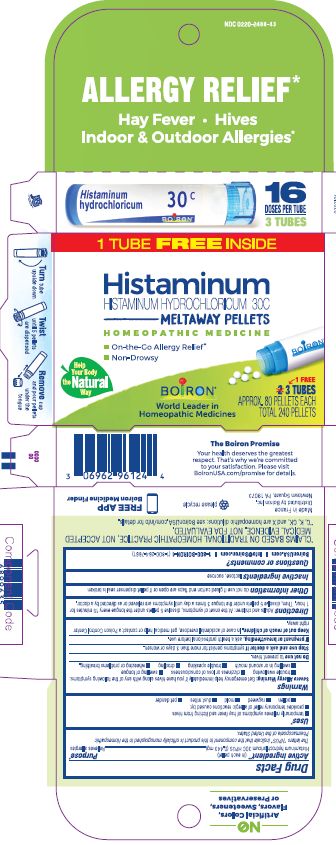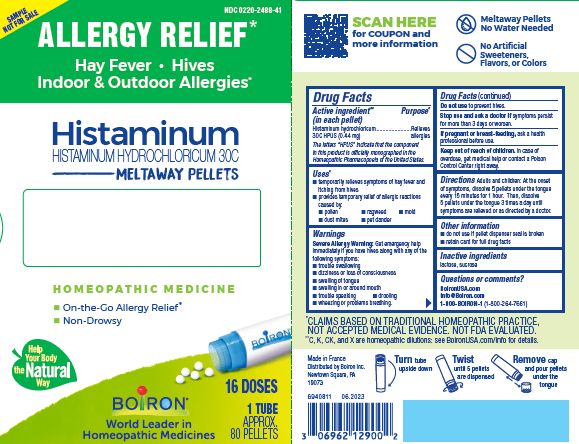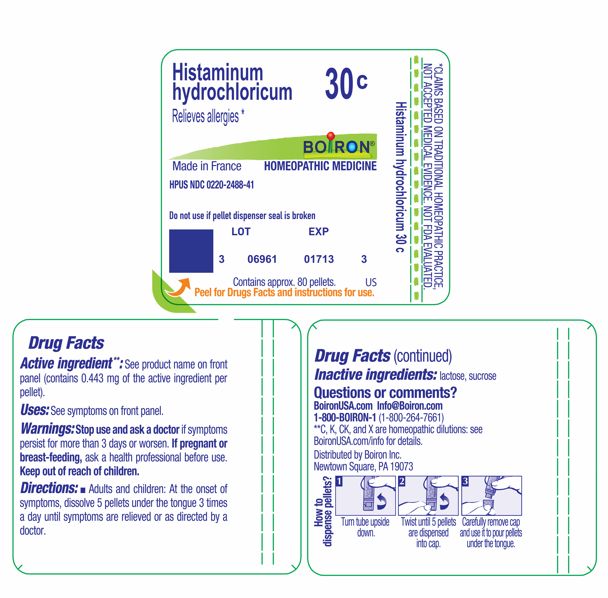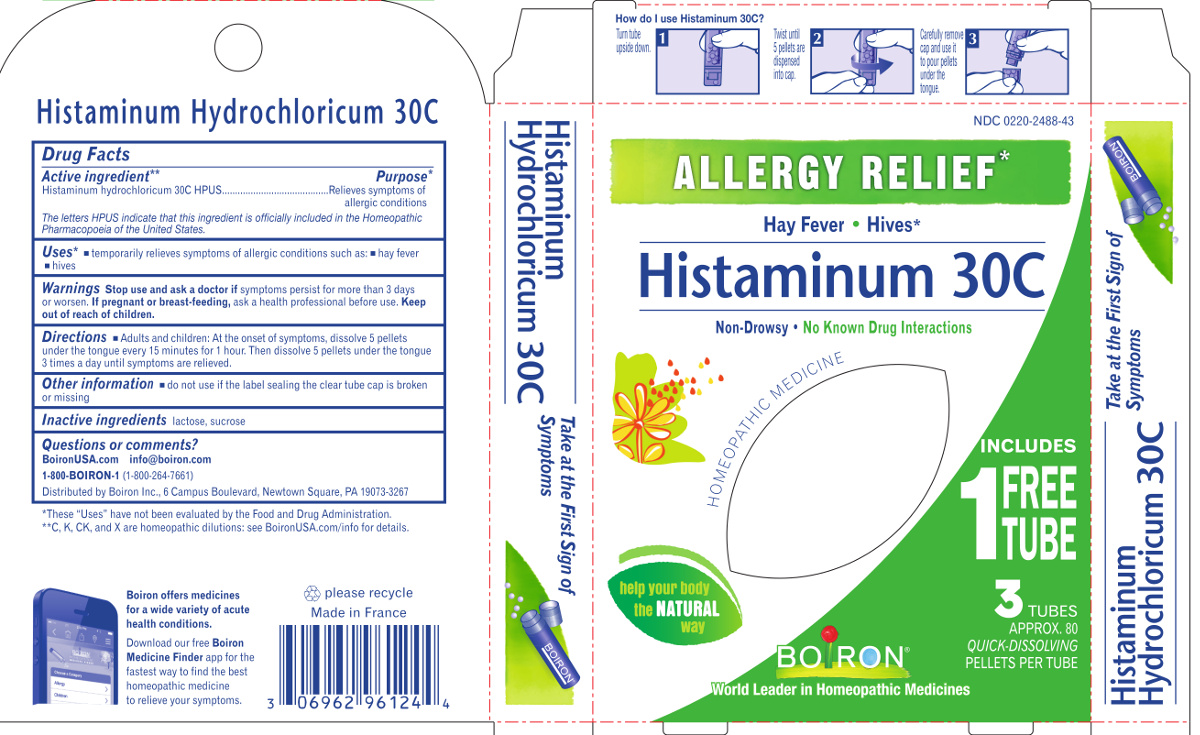 DRUG LABEL: Histaminum 30C Allergy Relief
NDC: 0220-2488 | Form: PELLET
Manufacturer: Laboratoires Boiron
Category: homeopathic | Type: HUMAN OTC DRUG LABEL
Date: 20251031

ACTIVE INGREDIENTS: HISTAMINE DIHYDROCHLORIDE 30 [hp_C]/1 1
INACTIVE INGREDIENTS: SUCROSE; LACTOSE

Histaminum 30C Allergy Relief

Active ingredient** (in each pellet)

Histaminum Hydrochloricum 30C HPUS (0.44 mg)

The letters "HPUS" indicate that the component in this product are officially monographed in the Homeopathic Pharmacopoeia of the United States.

Purpose*

Histaminum hydrochloricum 30C HPUS (0.443 mg) ... Relieves allergies

Uses*

- temporarily relieves symptoms of hay fever and itching from hives
- provides temporary relief of allergic reactions caused by:

- pollen
- ragweed
- mold
- dust mites
- pet dander

WARNINGS

Severe Allergy Warning: Get emergency help immediately if you have hives along with any of the following symptoms:

- trouble swallowing
- dizziness or loss of consciousness
- swelling of tongue
- swelling in or around mouth
- trouble speaking
- drooling
- wheezing or problems breathing.

Do not use to prevent hives.

Stop use and ask a doctor if symptoms persist for more than 3 days or worsen.

PREGNANCY OR BREAST FEEDING

If pregnant or breast-feeding, ask a health professional before use.

Keep out of reach of children. In case of accidental overdose, get medical help or contact a Poison Control Center right away.

DOSAGE AND ADMINISTRATION

Directions Adults and children: At the onset of symptoms, dissolve 5 pellets under the tongue every 15 minutes for 1 hour. Then, dissolve 5 pellets under the tongue 3 times a day until symptoms are relieved or as directed by a doctor.

INACTIVE INGREDIENT

lactose, sucrose.

Questions, Comments?
www.BoironUSA.com
info@boiron.com

1-800-BOIRON-1 (1-800-264-7661)

Distributed by Boiron Inc.
Newtown Square, PA 19073-3267

Other information do not use if glued carton end flaps are open or if pellet dispenser seal is broken

3 Tubes

Approx. 80 pellets each

Total 240 pellets

16 Doses per tube

Turn tube upside down Twist until 5 pellets are dispensed Remove cap and pour pellets under the tongue

Meltaway pellets

Allergy relief*

On the go allergy relief*

Non-drowsy

Hay Fever Hives Indoor & Outdoor Allergies*

1 Tube

Do not use if pellet dispenser seal is broken.

Contains approx. 80 quick dissolving pellets per tube.
How to dispense pellets? Turn tube upside down. Twist until 5 pellets are dispensed into cap. Carefully remove the cap and use it to pour pellets under the tongue.

*CLAIMS BASED ON TRADITIONAL HOMEOPATHIC PRACTICE NOT ACCEPTED MEDICAL EVIDENCE. NOT FDA EVALUATED.
**C,K,CK, and X are homeopathic dilutions: see BoironUSA.com/info for details.